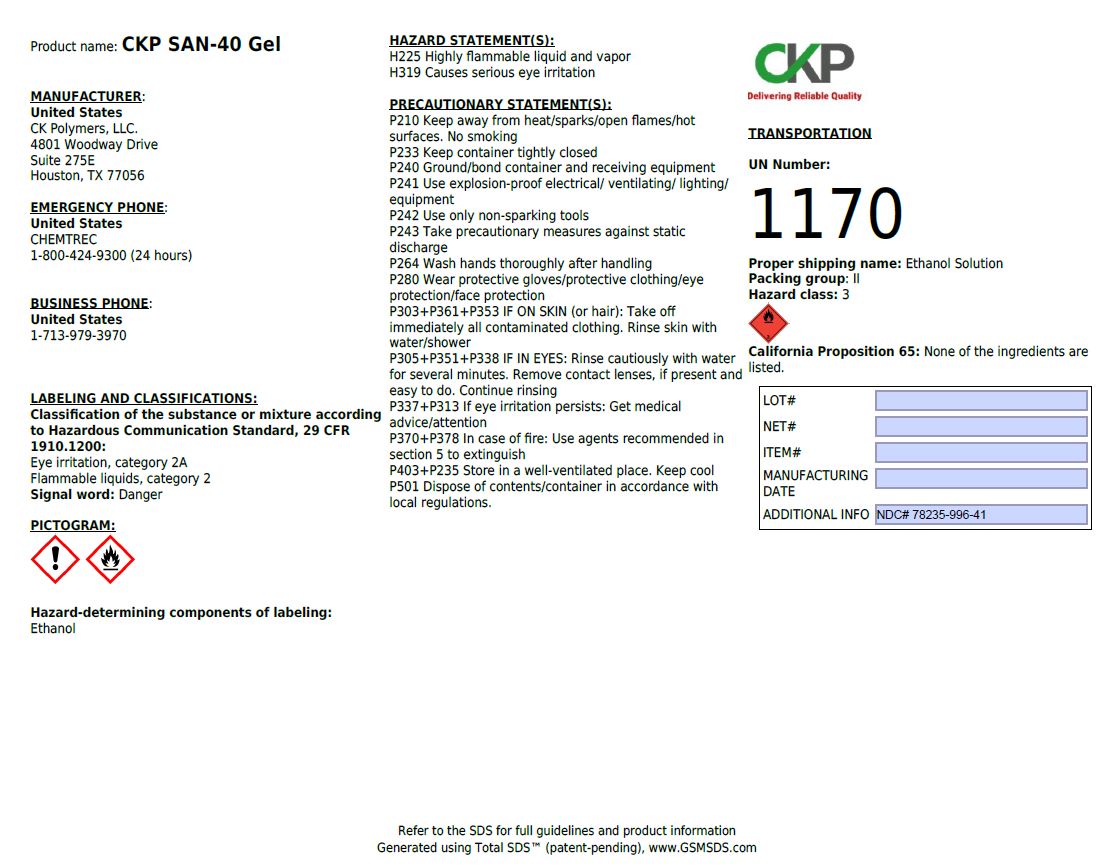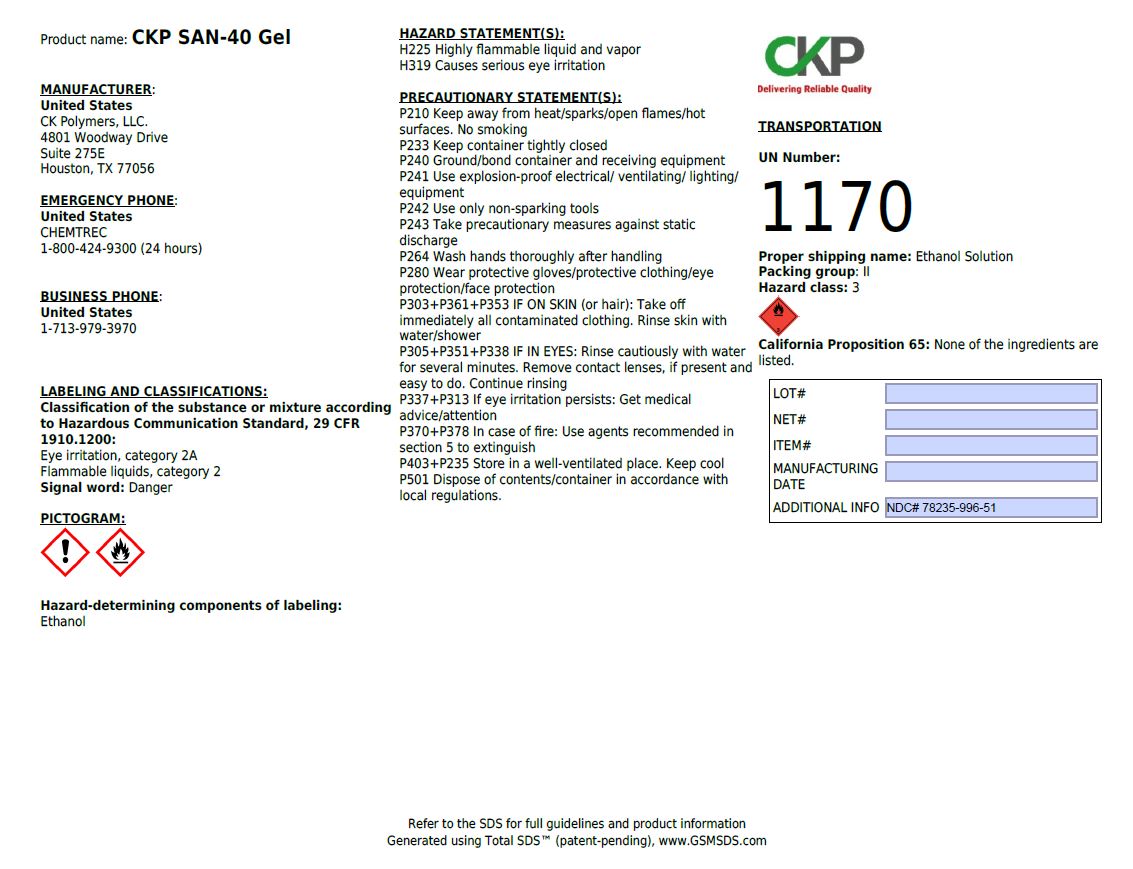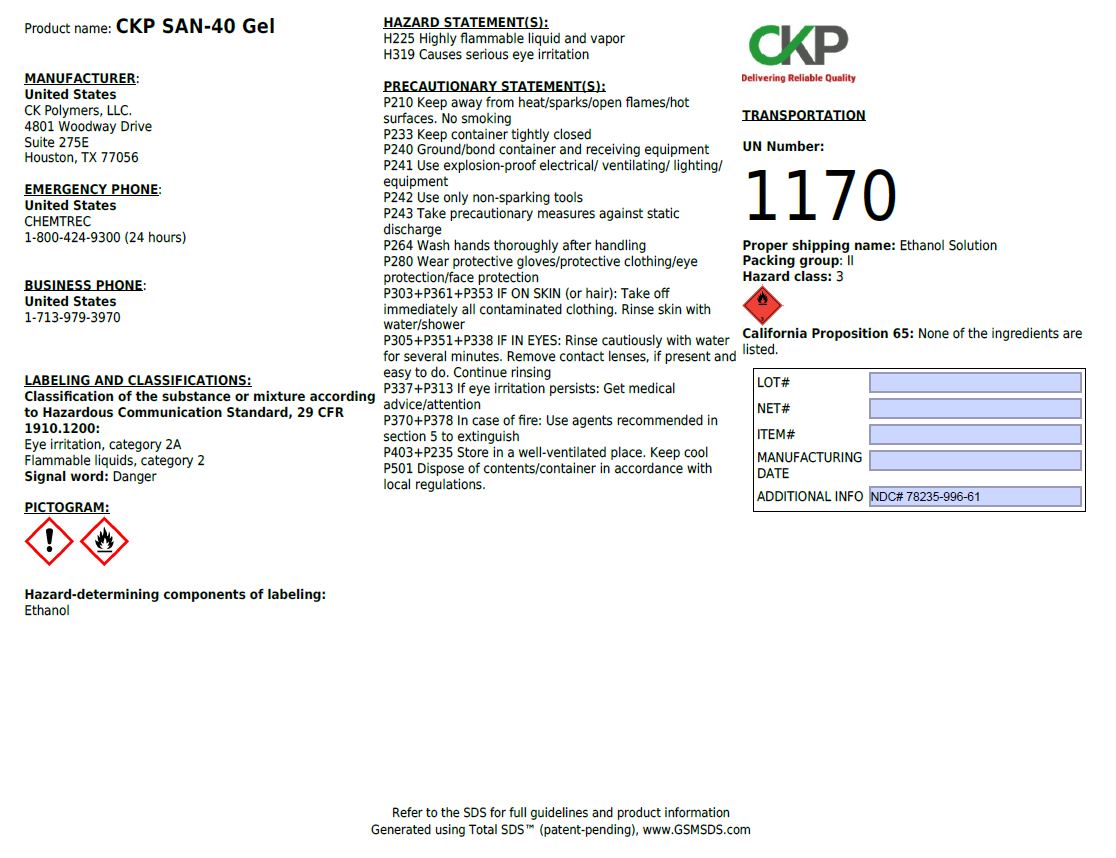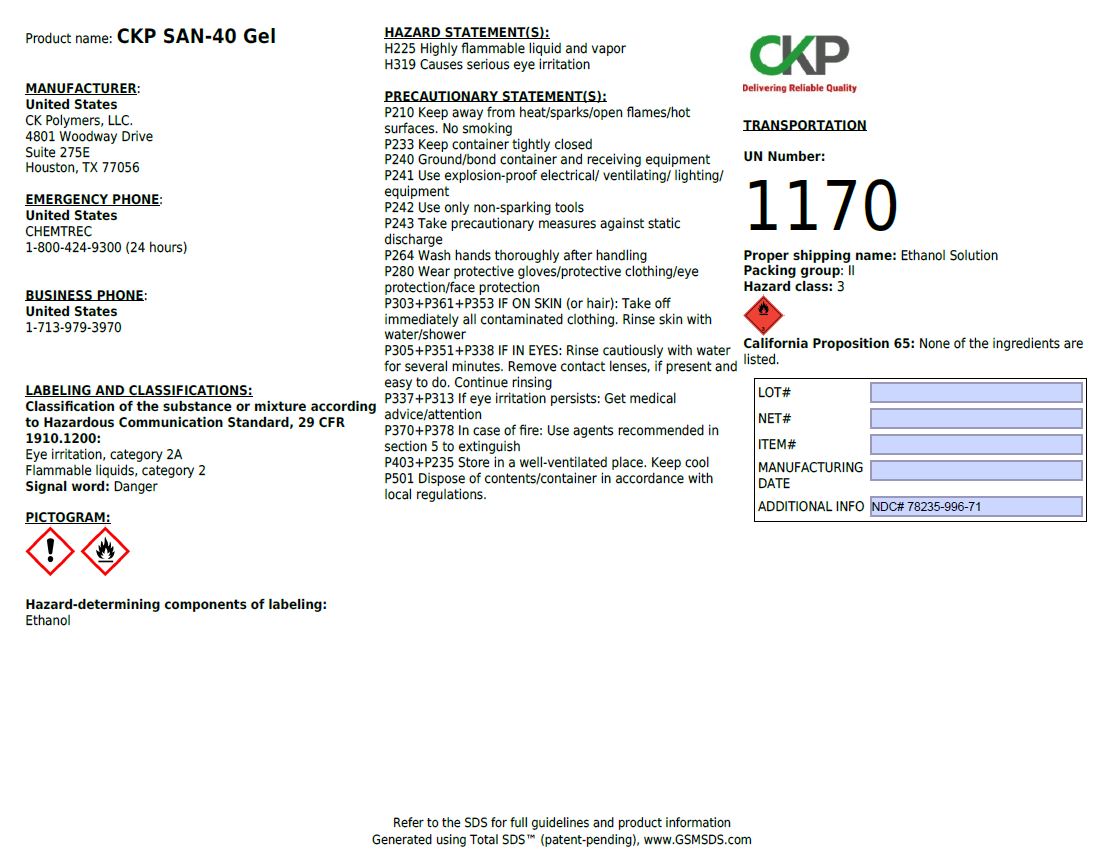 DRUG LABEL: CKP SAN-4I Liq
NDC: 78235-996 | Form: SOLUTION
Manufacturer: CK Polymers
Category: otc | Type: HUMAN OTC DRUG LABEL
Date: 20200702

ACTIVE INGREDIENTS: ALCOHOL 80 L/100 L
INACTIVE INGREDIENTS: GLYCERIN 1.45 L/100 L; HYDROGEN PEROXIDE 0.125 L/100 L; WATER 18.425 L/100 L

This is a hand sanitizer manufactured according to the Temporary Policy for Preparation of Certain Alcohol-Based Hand Sanitizer Products During the Public Health Emergency (CoViD-19); Guidance for Industry.

The hand sanitizer is manufactured using only the following United States Pharmacopoeia (USP) grade ingredients in the preparation of the product (percentage in final product formulation) consistent with World Health Organization (WHO) recommendations:

1. Alcohol (ethanol) (USP or Food Chemical Codex (FCC) grade) (80%, volume/volume (v/v)) in an aqueous solution denatured according to Alcohol and Tobacco Tax and Trade Bureau regulations in 27 CFR part 20.
2. Glycerol (1.45% v/v).
3. Hydrogen peroxide (0.125% v/v).
4. Sterile distilled water or boiled cold water.

The firm does not add other active or inactive ingredients. Different or additional ingredients may impact the quality and potency of the product.

Active Ingredient(s)

Alcohol 80% v/v. Purpose: Antiseptic

Purpose

Antiseptic, Hand Sanitizer

Use

Hand Sanitizer to help reduce bacteria that potentially can cause disease. For use when soap and water are not available.

Warnings

For external use only. Flammable. Keep away from heat or flame

Do not use

- in children less than 2 months of age
- on open skin wounds

When using this product keep out of eyes, ears, and mouth. In case of contact with eyes, rinse eyes thoroughly with water.
Stop use and ask a doctor if irritation or rash occurs. These may be signs of a serious condition.
Keep out of reach of children. If swallowed, get medical help or contact a Poison Control Center right away.

Stop use and ask a doctor if irritation or rash occurs. These may be signs of a serious condition.

Keep out of reach of children. If swallowed, get medical help or contact a Poison Control Center right away.

Directions

- Place enough product on hands to cover all surfaces. Rub hands together until dry.
- Supervise children under 6 years of age when using this product to avoid swallowing.

Other information

- Store between 15-30C (59-86F)
- Avoid freezing and excessive heat above 40C (104F)

Inactive ingredients

glycerin, hydrogen peroxide, purified water USP

Package Label - Principal Display Panel

1 L (1000 mL) NDC: 78235-996-41

MANUFACTURER:

United States

CK Polymers, LLC

4801 Woodway Drive

Suite 275E

Houston, TX 77056

EMERGENCY PHONE:

United States

CHEMTREC

1-800-424-9300 (24 hours)

BUSINESS PHONE:

United States

1-713-979-3970

LABELING AND CLASSIFICATIONS:

Classification of the substance or mixture according to Hazardous Communication Standard, 29 CFR 1910.1200:

Eye irritation, category 2A

Flammable liquids, category 2

Signal word: Danger

Hazard-determining components of labeling:

Ethanol

HAZARD STATEMENTS:

H224 Highly flammable liquid and vapor

H319 Causes serious eye irritation

PRECAUTIONARY STATEMENTS:

P210 Keep away from heat/sparks/open flames/hot surfaces. No smoking

P233 Keep container tightly closed

P240 Ground/bond container and receiving equipment

P241 Use explosion-proof electrical/ventilating/lighting/equipment

P242 Use only non-sparking tools

P243 Take precautionary measures against static discharge

P264 Wash hands thoroughly after handling

P280 Wear protective gloves/protective clothing/eye protection/face protection

P303+P361+P353 IF ON SKIN (or hair): Take off immediately all contaminated clothing. Rinse skin with water/shower.

P305+P351+P338 IF IN EYES: Rinse cautiously with water for several minutes. Remove contact lenses, if present and easy to do. Continue rinsing

P337+P313 If eye irritation persists: Get medical advice/attention

P370+P378 In case of fire: Use agents recommended in section 5 to extinguish

P403+P235 Store in a well-ventilated place. Keep cool

P501 Dispose of contents/container in accordance with local regulations.

TRANSPORTATION:

UN Number: 1170

Proper shipping name: Ethanol Solution

Packing group: II

Hazard class: 3

California Proposition 65: None of the ingredients are listed.

Refer to the SDS for full guidelines and product information

Generated using Total SDS (patent-pending), www.GSMSDS.com

NDC: 78235-996-51

NDC: 78235-996-61

NDC: 78235-996-71